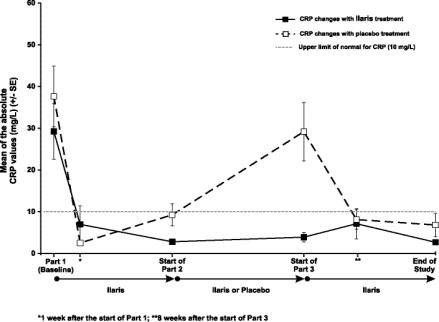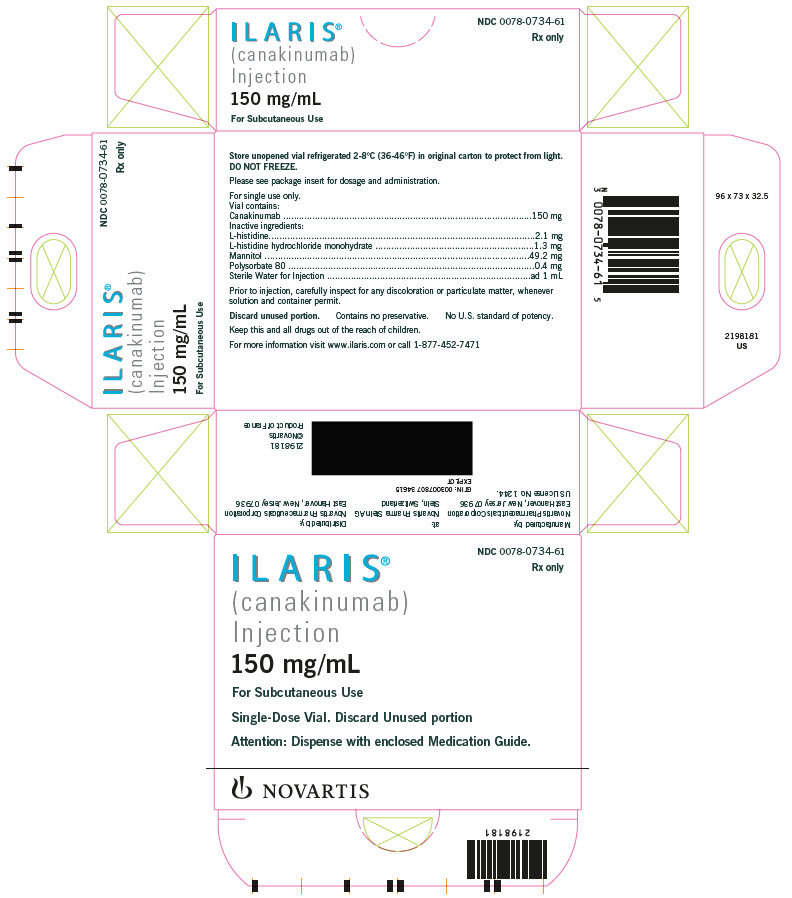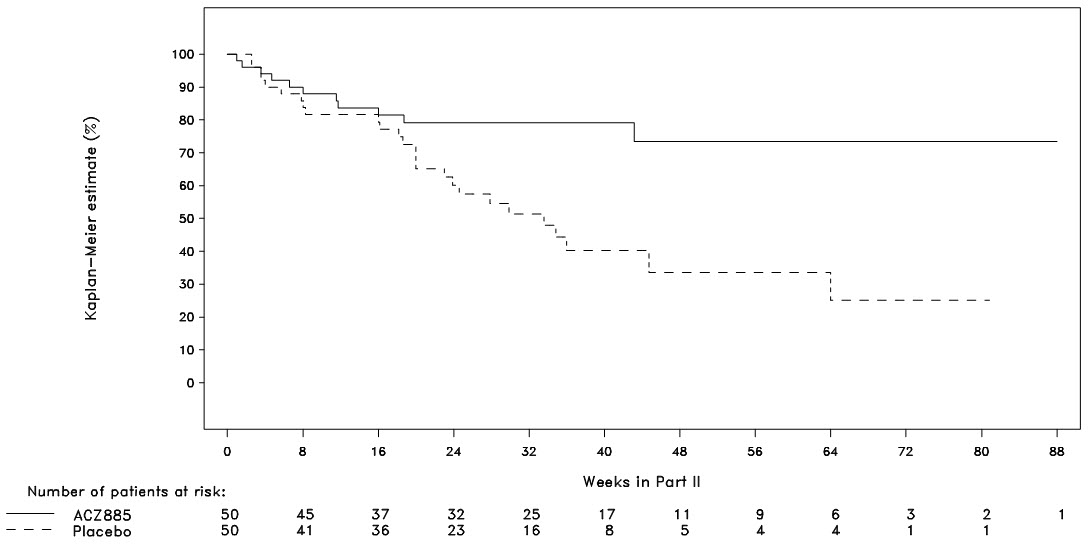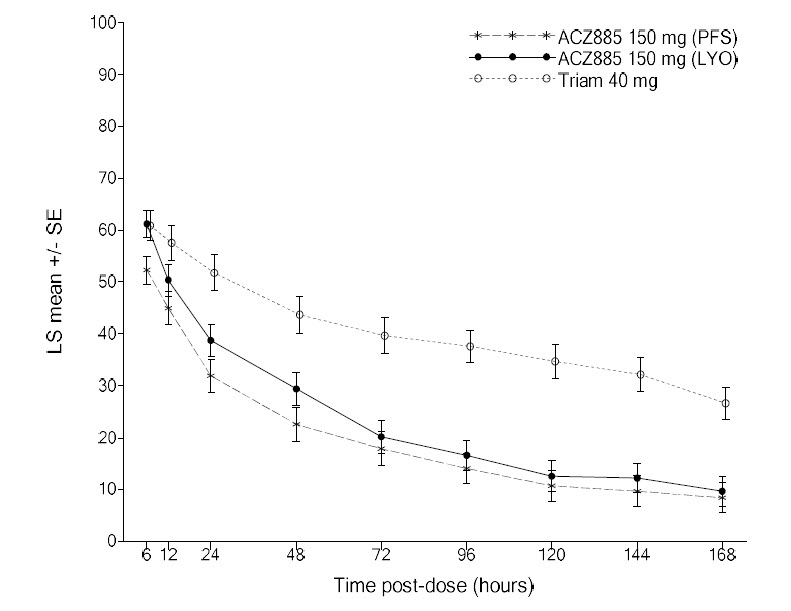 DRUG LABEL: Ilaris
NDC: 0078-0734 | Form: INJECTION, SOLUTION
Manufacturer: Novartis Pharmaceuticals Corporation
Category: prescription | Type: HUMAN PRESCRIPTION DRUG LABEL
Date: 20250618

ACTIVE INGREDIENTS: CANAKINUMAB 150 mg/1 mL
INACTIVE INGREDIENTS: HISTIDINE 2.1 mg/1 mL; HISTIDINE MONOHYDROCHLORIDE 1.3 mg/1 mL; MANNITOL 49.2 mg/1 mL; POLYSORBATE 80 0.4 mg/1 mL; WATER

HIGHLIGHTS OF PRESCRIBING INFORMATION

These highlights do not include all the information needed to use ILARIS safely and effectively. See full prescribing information for ILARIS.
ILARIS® (canakinumab) injection, for subcutaneous use
Initial U.S. Approval: 2009

RECENT MAJOR CHANGES

Warnings and Precautions, Hypersensitivity Reactions (5.3) | 11/2024

1 INDICATIONS AND USAGE

ILARIS is an interleukin-1β blocker indicated for the treatment of:

• Periodic Fever Syndromes (1.1):

- Cryopyrin-Associated Periodic Syndromes (CAPS), in adults and children 4 years of age and older, including:

◾ Familial Cold Auto-inflammatory Syndrome (FCAS)

◾ Muckle-Wells Syndrome (MWS)

- Tumor Necrosis Factor Receptor Associated Periodic Syndrome (TRAPS) in adult and pediatric patients

- Hyperimmunoglobulin D Syndrome (HIDS)/Mevalonate Kinase Deficiency (MKD) in adult and pediatric patients

- Familial Mediterranean Fever (FMF) in adult and pediatric patients

• Active Still’s Disease, including Adult-Onset Still’s Disease (AOSD) and Systemic Juvenile Idiopathic Arthritis (SJIA) in patients 2 years of age and older (1.2)

• Gout flares in adults in whom non-steroidal anti-inflammatory drugs (NSAIDs) and colchicine are contraindicated, are not tolerated, or do not provide an adequate response, and in whom repeated courses of corticosteroids are not appropriate (1.3)

2 DOSAGE AND ADMINISTRATION

• CAPS: Recommended weight-based dosage is:

- For patients > 40 kg: 150 mg subcutaneously, every 8 weeks

- For patients ≥ 15 kg and < 40 kg: 2 mg/kg subcutaneously, every 8 weeks. For pediatric patients 15 kg to 40 kg with an inadequate response, the dose can be increased to 3 mg/kg. (2.2)

• TRAPS, HIDS/MKD, and FMF: Recommended weight-based dosage is:

- For patients > 40 kg: Starting dosage is 150 mg subcutaneously every 4 weeks. The dosage can be increased to 300 mg every 4 weeks if the clinical response is not adequate. (2.3)

- For patients ≤ 40 kg: Starting dosage is 2 mg/kg subcutaneously every 4 weeks. The dosage can be increased to 4 mg/kg every 4 weeks if the clinical response is not adequate. (2.3)

- Still’s disease (AOSD and SJIA): Recommended weight-based dosage for patients ≥ 7.5 kg is 4 mg/kg (maximum dose of 300 mg), subcutaneously, every 4 weeks. (2.4)
- Gout Flares: Recommended dosage is 150 mg subcutaneously. In patients who require re-treatment, there should be an interval of at least 12 weeks before a new dose of ILARIS may be administered. (2.5)

3 DOSAGE FORMS AND STRENGTHS

- Injection: 150 mg/mL solution in single-dose vials. (3)

4 CONTRAINDICATIONS

Confirmed hypersensitivity to canakinumab or to any of the excipients. (4)

5 WARNINGS AND PRECAUTIONS

- Serious Infections: ILARIS has been associated with an increased incidence of serious infections. Exercise caution when administering ILARIS to patients with infections, a history of recurring infections or underlying conditions which may predispose them to infections. Discontinue ILARIS if a patient develops a serious infection. Avoid administering ILARIS to patients during an active infection requiring medical intervention. (5.1)
- Hypersensitivity Reactions and Drug Reaction with Eosinophilia and Systemic Symptoms (DRESS) can occur; discontinue ILARIS, treat promptly, and monitor until reaction resolves. (5.3)
- Immunizations: Avoid administration of live vaccines concurrently with ILARIS. Update all recommended vaccinations prior to initiation of therapy with ILARIS. (5.4)

6 ADVERSE REACTIONS

- CAPS: The most common adverse reactions (>10%) are nasopharyngitis, diarrhea, influenza, rhinitis, nausea, headache, bronchitis, gastroenteritis, pharyngitis, weight increased, musculoskeletal pain, and vertigo. (6)
- TRAPS, HIDS/MKD, and FMF: The most common adverse reactions (≥10%) are injection-site reactions and nasopharyngitis. (6)
- Still’s Disease: The most common adverse drug reactions (>10%) are infections (nasopharyngitis and upper respiratory tract infections), abdominal pain, and injection-site reactions. (6)
- Gout Flares: The most common adverse reactions (>2%) reported by are nasopharyngitis, upper respiratory tract infections, urinary tract infections, hypertriglyceridemia, and back pain. (6)

To report SUSPECTED ADVERSE REACTIONS, contact Novartis Pharmaceuticals Corporation at 1-888-669-6682 or FDA at 1-800-FDA-1088 or www.fda.gov/medwatch.

FULL PRESCRIBING INFORMATION

1 INDICATIONS AND USAGE

1.1 Periodic Fever Syndromes

ILARIS® (canakinumab) is an interleukin-1β (IL-1β) blocker indicated for the treatment of the following autoinflammatory Periodic Fever Syndromes:

Cryopyrin-Associated Periodic Syndromes (CAPS)

ILARIS is indicated for the treatment of Cryopyrin-Associated Periodic Syndromes (CAPS), in adults and pediatric patients 4 years of age and older, including:

- Familial Cold Autoinflammatory Syndrome (FCAS)
- Muckle-Wells Syndrome (MWS)

Tumor Necrosis Factor Receptor (TNF) Associated Periodic Syndrome (TRAPS)

ILARIS is indicated for the treatment of Tumor Necrosis Factor (TNF) Receptor Associated Periodic Syndrome (TRAPS) in adult and pediatric patients.

Hyperimmunoglobulin D Syndrome (HIDS)/Mevalonate Kinase Deficiency (MKD)

ILARIS is indicated for the treatment of Hyperimmunoglobulin D (Hyper-IgD) Syndrome (HIDS)/Mevalonate Kinase Deficiency (MKD) in adult and pediatric patients.

Familial Mediterranean Fever (FMF)

ILARIS is indicated for the treatment of Familial Mediterranean Fever (FMF) in adult and pediatric patients.

1.2 Still’s Disease (Adult-Onset Still’s Disease [AOSD] and Systemic Juvenile Idiopathic Arthritis [SJIA])

ILARIS is indicated for the treatment of active Still’s Disease, including Adult-Onset Still’s Disease (AOSD) and Systemic Juvenile Idiopathic Arthritis (SJIA) in patients 2 years of age and older.

1.3 Gout Flares

ILARIS is indicated for the symptomatic treatment of adult patients with gout flares in whom non-steroidal anti-inflammatory drugs (NSAIDs) and colchicine are contraindicated, are not tolerated, or do not provide an adequate response, and in whom repeated courses of corticosteroids are not appropriate.

2 DOSAGE AND ADMINISTRATION

2.1 General Dosing Information

ILARIS IS FOR SUBCUTANEOUS USE ONLY.

2.2 Recommended Dosage for Cryopyrin-Associated Periodic Syndromes (CAPS)

The recommended weight-based dosage of ILARIS is:

- For patients with CAPS > 40 kg: 150 mg subcutaneously, every 8 weeks
- For patients with CAPS ≥ 15 kg and ≤ 40 kg: 2 mg/kg subcutaneously, every 8 weeks.
- For pediatric patients with CAPS 15 kg to 40 kg with an inadequate response, the dosage can be increased to 3 mg/kg subcutaneously, every 8 weeks.

2.3 Recommended Dosage for Tumor Necrosis Factor Receptor Associated Periodic Syndrome (TRAPS), Hyperimmunoglobulin D Syndrome/Mevalonate Kinase Deficiency (HIDS/MKD), and Familial Mediterranean Fever (FMF)

The recommended weight-based dosage of ILARIS for patients with TRAPS, HIDS/MKD, and FMF is:

- For patients > 40 kg: 150 mg subcutaneously, every 4 weeks. The dosage can be increased to 300 mg every 4 weeks if the clinical response is not adequate.
- For patients ≤ 40 kg: 2 mg/kg administered subcutaneously, every 4 weeks. The dosage can be increased to 4 mg/kg every 4 weeks if the clinical response is not adequate.

2.4 Recommended Dosage for Still’s Disease, Including Adult-Onset Still’s Disease (AOSD) and Systemic Juvenile Idiopathic Arthritis (SJIA)

The recommended weight-based dosage of ILARIS for patients with Still’s Disease (AOSD and SJIA) weighing ≥ 7.5 kg is 4 mg/kg (maximum dose of 300 mg) administered subcutaneously every 4 weeks.

2.5 Recommended Dosage for Gout Flares

The recommended dose of ILARIS for adult patients with a gout flare is 150 mg administered subcutaneously. In patients who require re-treatment, there should be an interval of at least 12 weeks before a new dose of ILARIS may be administered.

2.6 Administration Instructions for ILARIS Injection

STEP 1: ILARIS injection has a concentration of 150 mg/mL. Do not shake. The solution should be essentially free from particulates, clear to opalescent, colorless to slightly brownish-yellow tint. If the solution has a distinctly brown discoloration, is highly opalescent or contains visible particles, do not use.

STEP 2: Using a sterile 1-mL syringe and 18-gauge x 2” needle, carefully withdraw the required volume depending on the dose to be administered and subcutaneously inject using a 27-gauge x 0.5” needle.

Avoid injection into scar tissue as this may result in insufficient exposure to ILARIS.

Discard unused product or waste material in accordance with the local requirements.

3 DOSAGE FORMS AND STRENGTHS

Injection: 150 mg/mL, clear to slightly opalescent, colorless to a slightly brownish yellow tint solution, in single-dose vials.

4 CONTRAINDICATIONS

Confirmed hypersensitivity to canakinumab or to any of the excipients [see Warnings and Precautions (5.3) and Adverse Reactions (6.1)].

5 WARNINGS AND PRECAUTIONS

5.1 Serious Infections

ILARIS has been associated with an increased risk of serious infections. Exercise caution when administering ILARIS to patients with infections, a history of recurring infections or underlying conditions which may predispose them to infections. Avoid administering ILARIS to patients during an active infection requiring medical intervention. Discontinue ILARIS if a patient develops a serious infection.

Infections, predominantly of the upper respiratory tract, in some instances serious, have been reported with ILARIS. Generally, the observed infections responded to standard therapy. Isolated cases of unusual or opportunistic infections (e.g., aspergillosis, atypical mycobacterial infections, cytomegalovirus, herpes zoster) were reported during ILARIS treatment. A causal relationship of ILARIS to these events cannot be excluded. In clinical trials, ILARIS has not been administered concomitantly with tumor necrosis factor (TNF) inhibitors. An increased incidence of serious infections has been associated with administration of another IL-1 blocker in combination with TNF inhibitors. Coadministration of ILARIS with TNF inhibitors is not recommended because this may increase the risk of serious infections [see Drug Interactions (7.1)].

Drugs that affect the immune system by blocking TNF have been associated with an increased risk of new tuberculosis and reactivation of latent tuberculosis (TB). It is possible that use of IL-1 inhibitors, such as ILARIS, increases the risk of reactivation of tuberculosis or of opportunistic infections.

Prior to initiating immunomodulatory therapies, including ILARIS, evaluate patients for active and latent tuberculosis infection. Appropriate screening tests should be performed in all patients. ILARIS has not been studied in patients with a positive tuberculosis screen, and the safety of ILARIS in individuals with latent tuberculosis infection is unknown. Treat patients testing positive in tuberculosis screening according to standard medical practice prior to therapy with ILARIS. Instruct patients to seek medical advice if signs, symptoms, or high-risk exposure suggestive of tuberculosis (e.g., persistent cough, weight loss, subfebrile temperature) appear during or after ILARIS therapy.

Healthcare providers should follow current CDC guidelines both to evaluate for and to treat possible latent tuberculosis infections before initiating therapy with ILARIS.

5.2 Immunosuppression

The impact of treatment with anti-interleukin-1 (IL-1) therapy on the development of malignancies is not known. However, treatment with immunosuppressants, including ILARIS, may result in an increase in the risk of malignancies.

5.3 Hypersensitivity Reactions

Hypersensitivity reactions have been reported with ILARIS. During clinical trials, no anaphylactic reactions attributable to treatment with canakinumab have been reported. It should be recognized that symptoms of the underlying disease being treated may be similar to symptoms of hypersensitivity [see Adverse Reactions (6.1)]. Drug Reaction with Eosinophilia and Systemic Symptoms (DRESS), characterized by serious skin eruptions, has been reported in patients with autoinflammatory conditions treated with ILARIS. If a severe hypersensitivity reaction occurs, immediately discontinue ILARIS; treat promptly and monitor until signs and symptoms resolve.

5.4 Immunizations

Avoid administration of live vaccines concurrently with ILARIS [see Drug Interactions (7.2)]. Since no data are available on either the efficacy or on the risks of secondary transmission of infection by live vaccines in patients receiving ILARIS, avoid administering live vaccines concurrently with ILARIS. In addition, because ILARIS may interfere with normal immune response to new antigens, vaccinations may not be effective in patients receiving ILARIS. Limited data are available on the response to vaccinations with inactivated (killed) antigens in patients receiving ILARIS [see Drug Interactions (7.2)].

Because IL-1 blockade may interfere with immune response to infections, it is recommended that prior to initiation of therapy with ILARIS, adult and pediatric patients receive all recommended vaccinations, as appropriate and if feasible, including pneumococcal vaccine and inactivated influenza vaccine. See current recommended immunization schedules at the website of the Centers for Disease Control, http://www.cdc.gov/vaccines/schedules/index.html.

5.5 Macrophage Activation Syndrome

Macrophage activation syndrome (MAS) is a known, life-threatening disorder that may develop in patients with rheumatic conditions, in particular Still’s disease, and should be aggressively treated. Physicians should be attentive to symptoms of infection or worsening of Still’s disease, as these are known triggers for MAS. Eleven cases of MAS were observed in 201 SJIA patients treated with canakinumab in clinical trials. Based on the clinical trial experience, ILARIS does not appear to increase the incidence of MAS in Still’s disease patients, but no definitive conclusion can be made.

6 ADVERSE REACTIONS

The following clinically significant adverse reactions are described elsewhere in the labeling:

- Serious Infections [see Warnings and Precautions (5.1)]
- Immunosuppression [see Warnings and Precautions (5.2)]
- Hypersensitivity Reactions [see Warnings and Precautions (5.3)]
- Macrophage Activation Syndrome [see Warnings and Precautions (5.5)]

6.1 Clinical Trials Experience

Because clinical trials are conducted under widely varying conditions, adverse reaction rates observed in the clinical trials of a drug cannot be directly compared to rates in the clinical trials of another drug and may not reflect the rates observed in practice.

Adverse Reactions from Clinical Trials for Treatment of Periodic Fever Syndromes: CAPS, TRAPS, HIDS/MKD, and FMF

Treatment of CAPS

The data described herein reflect exposure to ILARIS in 104 adult and pediatric CAPS patients, including 20 FCAS, 72 MWS, 10 MWS/NOMID (Neonatal Onset Multisystem Inflammatory Disorder) overlap, 1 non-FCAS non-MWS, and 1 misdiagnosed in placebo-controlled (35 patients) and uncontrolled trials. Sixty-two patients were exposed to ILARIS for at least 6 months, 56 for at least 1 year, and 4 for at least 3 years. A total of 9 serious adverse reactions were reported for CAPS patients. Among these were vertigo (2 patients), infections (3 patients), including intra-abdominal abscess following appendectomy (1 patient). The most commonly reported adverse reactions associated with ILARIS treatment in greater than 10% of the CAPS patients were nasopharyngitis, diarrhea, influenza, rhinitis, nausea, headache, bronchitis, gastroenteritis, pharyngitis, weight increased, musculoskeletal pain, and vertigo. One patient discontinued treatment due to potential infection.

CAPS Study 1 investigated the safety of ILARIS in an 8-week, open-label period (Part 1), followed by a 24-week, randomized withdrawal period (Part 2), followed by a 16-week, open-label period (Part 3). All patients were treated with ILARIS 150 mg subcutaneously or 2 mg/kg if body weight was greater than or equal to 15 kg and less than or equal to 40 kg (see Table 1).

Since all CAPS patients received ILARIS in Part 1, there are no controlled data on adverse events (AEs). Data in Table 1 are for all AEs for all CAPS patients receiving canakinumab. In CAPS Study 1, no pattern was observed for any type or frequency of adverse events throughout the 3 study periods.

Table 1: Adverse Reactions in ≥ 10% of Patients in Parts 1 to 3 of the Phase 3 Trial for Patients with CAPS
Adverse reactions | ILARIS N = 35 n (%)
n (%) of patients with adverse reactions | 35 (100)
Nasopharyngitis | 12 (34)
Diarrhea | 7 (20)
Influenza | 6 (17)
Rhinitis | 6 (17)
Nausea | 5 (14)
Headache | 5 (14)
Bronchitis | 4 (11)
Gastroenteritis | 4 (11)
Pharyngitis | 4 (11)
Weight increased | 4 (11)
Musculoskeletal pain | 4 (11)
Vertigo | 4 (11)

Vertigo

Vertigo has been reported in 9% to 14% of patients in CAPS studies, exclusively in MWS patients, and reported as a serious adverse event in 2 cases. All events resolved with continued treatment with ILARIS.

Injection-Site Reactions

In CAPS Study 1, subcutaneous injection-site reactions were observed in 9% of patients in Part 1 with mild tolerability reactions; in Part 2, one patient each (7%) had a mild or a moderate tolerability reaction and, in Part 3, one patient had a mild local tolerability reaction. No severe injection-site reactions were reported, and none led to discontinuation of treatment.

Treatment of TRAPS, HIDS/MKD, and FMF

A Phase 3 trial (TRAPS, HIDS/MKD, and FMF Study 1) investigated the safety of ILARIS in 3 cohorts (TRAPS, HIDS/MKD, and FMF) as follows: a 12-week screening period (Part 1), followed by a 16-week, randomized, double-blind, placebo-controlled parallel-arm treatment period (Part 2), followed by a 24-week randomized withdrawal period (Part 3), followed by a 72-week, open-label treatment period (Part 4). All patients randomized to treatment with ILARIS in Part 2 received 150 mg subcutaneously every 4 weeks if body weight was greater than 40 kg (or 2 mg/kg every 4 weeks if body weight was less than or equal to 40 kg).

In Part 2 of the TRAPS, HIDS/MKD, and FMF Study 1, initially 90 patients were randomized to ILARIS treatment, and 91 patients were randomized to placebo. Of patients randomized to ILARIS, 55.6% remained on the initial dose through Week 16 with 6.7% receiving an additional ILARIS dose between Day 7 and Day 15. Of the patients randomized to placebo, 9.9% remained on placebo through Week 16 with 28.6% switching to active treatment with ILARIS by Day 15.

Overall, there were 43 TRAPS, 68 HIDS/MKD, and 58 FMF patients in the safety set with a cumulative canakinumab exposure of 47.61 patient-years. The cumulative exposure in the placebo group was 8.03 patient-years.

In Part 2 of the TRAPS, HIDS/MKD, and FMF Study 1, a total of 22 TRAPS patients aged 3 to 76 years of age, 37 HIDS/MKD patients aged 2 to 43 years of age, and 31 FMF patients aged 2 to 60 years of age were initially randomized to treatment with ILARIS 150 mg every four weeks in the placebo-controlled period of the clinical trial. In addition, 4 non-randomized patients (2 FMF patients of age 20 and 29 years with non-exon 10 mutations and 2 HIDS/MKD patients both of 1 year of age) received open-label treatment in Part 2.

The most commonly reported adverse reactions (greater than or equal to 10%) associated with ILARIS treatment in TRAPS, HIDS/MKD, and FMF patients were injection-site reactions and nasopharyngitis. The reported adverse reactions (greater than or equal to 3%) associated with ILARIS treatment in TRAPS, HIDS/MKD, and FMF patients were injection-site reactions (10.1%), and infections, including nasopharyngitis (10.7%), upper respiratory tract infection (7.1%), rhinitis (5.3%), gastroenteritis (3.0%), and pharyngitis (3.0%). Serious infections (e.g., conjunctivitis, pneumonia, pharyngitis, pharyngotonsillitis) were observed in approximately 2.4% (0.03 per 100 patient-days) of patients receiving ILARIS in Part 2 of the TRAPS, HIDS/MKD, and FMF Study 1.

In the ILARIS treatment group, 1 TRAPS patient discontinued treatment due to adverse events, 2 HIDS/MKD patients discontinued treatment due to adverse events, and no FMF patients discontinued treatment due to an adverse event.

Injection-Site Reactions

In the TRAPS, HIDS/MKD, and FMF Study 1, subcutaneous injection-site reactions were observed in 10.1% of patients in Part 2 who had a mild or a moderate tolerability reaction. No severe injection-site reactions were reported and none led to discontinuation of treatment.

Adverse Reactions from Clinical Trials for Treatment of Still’s Disease: SJIA and AOSD

The safety of ILARIS compared to placebo in SJIA patients was investigated in two Phase 3 studies [see Clinical Studies (14.2)]. Patients in SJIA Study 1 received a single dose of ILARIS 4 mg/kg (n = 43) or placebo (n = 41) via subcutaneous injection and were assessed at Day 15 for the efficacy endpoints and had a safety analysis up to Day 29. SJIA Study 2 was a two-part study with an open-label, single-arm active treatment period (Part I) followed by a randomized, double-blind, placebo-controlled, event-driven withdrawal design (Part II). Overall, 177 patients were enrolled into the study and received ILARIS 4 mg/kg (up to 300 mg maximum) in Part I, and 100 patients received ILARIS 4 mg/kg (up to 300 mg maximum) every 4 weeks or placebo in Part II. Adverse drug reactions listed in Table 2 showed higher rates than placebo from both trials. The adverse drug reactions associated with ILARIS treatment in greater than 10% of SJIA patients were infections, abdominal pain, and injection-site reactions. Serious infections (e.g., pneumonia, varicella, gastroenteritis, measles, sepsis, otitis media, sinusitis, adenovirus, lymph node abscess, pharyngitis) were observed in approximately 4% to 5% (0.02 to 0.17 per 100 patient-days) of patients receiving ILARIS in both studies.

Table 2: Tabulated Summary of Adverse Drug Reactions From Pivotal SJIA Clinical Trials
 |  | SJIA Study 2 |  |  | SJIA Study 1
 |  | Part I | Part II
 |  | ILARIS N = 177 n (%) (IR)^ | ILARIS N = 50 n (%) (IR) | Placebo N = 50 n (%) (IR) | ILARIS N = 43 n (%) (IR) | Placebo N = 41 n (%) (IR)
Infections and infestations
All infections (e.g., nasopharyngitis, [viral] upper respiratory tract infection, pneumonia, rhinitis, pharyngitis, tonsillitis, sinusitis, urinary tract infection, gastroenteritis, viral infection) | 97 (54.8%) (0.91) |  | 27 (54%) (0.59) | 19 (38%) (0.63) | 13 (30.2%) (1.26) |  | 5 (12.2%) (1.37)
Gastrointestinal disorders
Abdominal pain (upper) | 25 (14.1%) (0.16) |  | 8 (16%) (0.15) | 6 (12%) (0.08) | 3 (7%) (0.25) |  | 1 (2.4%) (0.23)
Skin and subcutaneous tissue disorders
Injection-site reaction*
mild | 19 (10.7%) |  | 6 (12.0%) | 2 (4.0%) | 0 |  | 3 (7.3%)
moderate | 2 (1.1%) |  | 1 (2.0%) | 0 | 0 |  | 0
n = number of patients.
^IR = Exposure adjusted incidence rate per 100 patient-days.
*No injection-site reaction led to study discontinuation.

The safety profile of ILARIS in AOSD patients in a randomized, double-blind, placebo-controlled study (GDE01T) in 36 adult patients (aged 22 to 70 years) was similar to what was observed in SJIA patients.

Adverse Reactions from Clinical Trials for Treatment of Gout Flares

The safety of ILARIS compared to triamcinolone acetonide in patients with gout flares was assessed in four 12-week randomized, double-blind, active-controlled Phase 3 studies [see Clinical Studies (14.4) for details of the studies supporting efficacy] and in two 12-week double-blind active-controlled extension studies. In the ILARIS treatment groups 512 patients were treated up to 12 weeks and 165 of these patients up to 24 weeks. In the triamcinolone acetonide groups, 381 patients were treated up to 12 weeks and 152 of these patients up to 24 weeks. Patients received a single dose of ILARIS 150 mg (n = 467) via subcutaneous injection or triamcinolone acetonide 40 mg (n = 279) via intramuscular injection. Upon a new flare, 85 and 152 patients received at least one additional dose of ILARIS and triamcinolone acetonide, respectively.

The most commonly reported adverse drug reactions were infections and infestations (see Table 3). The most common infections reported in more than 2% of patients in the ILARIS treatment groups were nasopharyngitis, upper respiratory tract infections, and urinary tract infections. The trends observed in all infections are aligned with the overall known safety profile of canakinumab. Serious adverse events were reported in 1.4% of the ILARIS-treated patients, all of which were single events. No serious adverse events were reported in the triamcinolone acetonide-treated group.

Of the ILARIS-treated patients, 17% were 65 years of age and older, including 3% who were 75 years of age and older. No new safety findings were observed between these patients compared to patients under 65 years of age [see Use in Specific Populations (8.5).

Table 3: Tabulated Summary of Adverse Drug Reactions From Pivotal Gout Flare Clinical Trials
System Organ Class Adverse reaction | ILARIS 150 mg *N = 552 n (%) (IR-w) | Triamcinolone acetonide 40 mg *N = 431 n (%) (IR-w)
Infections and infestations
All infections (e.g., nasopharyngitis, upper respiratory tract infection, urinary tract infections) | 90 (16.3%) (59.0) | 40 (9.3%) (32.1)
Investigations
Blood triglycerides increased | 7 (1.3%) (3.8) | 2 (0.5%) (1.3)
Platelet count decreased | 4 (0.7%) (2.5) | 1 (0.2%) (1.0)
Metabolism and nutrition disorders
Hypertriglyceridemia | 15 (2.7%) (9.5) | 4 (0.9%) (3)
Musculoskeletal and connective tissue disorders
Back pain | 17 (3.1%) (10.9) | 7 (1.6%) (6.2)
Nervous system disorders
Dizziness | 9 (1.6%) (5.8) | 2 (0.5%) (1.7)
Abbreviation: SOC, system organ class.
*N = Number of patients at study entry.
IR-w = Study size weighted incidence rate (i.e., number of patients with an event per 100 patient-years).

Specific Adverse Reactions from Clinical Trials

Hypersensitivity

During clinical trials, no anaphylactic reactions attributable to treatment with canakinumab have been reported. In CAPS trials one patient discontinued and in TRAPS, HIDS/MKD, FMF, Still’s disease, and gout trials no patients discontinued due to hypersensitivity reactions. ILARIS should not be administered to any patients with known clinical hypersensitivity to ILARIS [see Contraindications (4) and Warnings and Precautions (5.3)].

Laboratory Abnormalities

- Hematology

TRAPS, HIDS/MKD, and FMF

Overall, in the TRAPS, HIDS/MKD, and FMF Study 1, neutrophil count decreased (greater than or equal to Grade 2) was reported in 6.5% of patients and platelet count decreased (greater than or equal to Grade 2) was reported in 0.6% of patients.

SJIA

During clinical trials with ILARIS, mean values decreased for white blood cells, neutrophils and platelets.

In the randomized, placebo-controlled portion of SJIA Study 2, decreased white blood cell counts (WBC) less than or equal to 0.8 times lower limit of normal (LLN) were reported in 5 patients (10.4%) in the ILARIS group compared to 2 patients (4.0%) in the placebo group. Transient decreases in absolute neutrophil count (ANC) to less than 1 x 10^9/L were reported in 3 patients (6.0%) in the ILARIS group compared to 1 patient (2.0%) in the placebo group. One case of ANC less than 0.5x10^9/L was observed in the ILARIS group and none in the placebo group.

Mild (less than LLN and greater than 75 x 10^9/L) and transient decreases in platelet counts were observed in 3 (6.3%) ILARIS-treated patients versus 1 (2.0%) placebo-treated patient.

Gout Flares

In the pooled analysis of patients with gout flares from four 12-week randomized, double-blind, active-controlled Phase 3 studies and two 12-week active-controlled extension studies, transient cytopenias were observed. Leukopenia (WBC ≤ 0.8 x LLN) was reported in 6.4% of ILARIS-treated patients compared to 1.4% of triamcinolone acetonide-treated patients. Neutropenia (ANC < 0.9 x LLN) was reported in 15.9% of patients treated with ILARIS compared to 2.1% treated with triamcinolone acetonide. Thrombocytopenia (platelet counts < LLN) was observed in 16.3% of patients treated with ILARIS versus 12.5% of patients treated with triamcinolone acetonide.

- Uric Acid

Gout Flares

The proportion of patients with laboratory abnormalities (from normal at baseline to >ULN or from ≤9.9 mg/dl at baseline to > 9.9 mg/dl) and/or adverse reactions of increased uric acid levels were numerically higher in the ILARIS group (43.8% for ILARIS vs. 40.1% for (triamcinolone acetonide).

- Hepatic Transaminases

Elevations of transaminases (ALT/AST) have been observed in patients treated with ILARIS.

SJIA

In the randomized, placebo-controlled portion of SJIA Study 2, high ALT and/or AST ≥ 3 times upper limit of normal (ULN) were reported in 2 (4.1%) ILARIS-treated patients and 1 (2.0%) placebo patient. All patients had normal values at the next visit.

Gout Flares

In the randomized double-blind studies up to 24 weeks high ALT and AST ≥ 3 times upper limit of normal (ULN) were reported in 1.6% and 0.5% of ILARIS-treated patients respectively, and 2.6% and 1.9% of the triamcinolone acetonide-treated patients, respectively.

- Bilirubin

SJIA

Asymptomatic and mild elevations of serum bilirubin have been observed in patients treated with ILARIS without concomitant elevations of transaminases.

- Hypertriglyceridemia

Gout Flares

The proportion of patients with hypertriglyceridemia events in the randomized double-blind studies up to 24 weeks was higher in the ILARIS group compared to the triamcinolone acetonide-treated group (5.6% vs. 1.9%). The majority of abnormal values were noted at a single visit.

6.2 Immunogenicity

A biosensor binding assay or a bridging immunoassay was used to detect antibodies directed against canakinumab in patients who received ILARIS. Following treatment with ILARIS, antibodies against ILARIS were observed in approximately 1.4%, 1.2%, and 3.5% of the patients with CAPS, SJIA, and gout flares, respectively. Neutralizing antibodies were detected in < 1% of patients with gout flares. No apparent correlation of antibody development to clinical response or adverse events was observed. The CAPS clinical studies employed the biosensor binding assay, most of the SJIA clinical studies employed the bridging assay, and the gout clinical studies used initially the biosensor assay and for later studies or extensions the bridging assay. The data obtained in an assay are highly dependent on several factors, including assay sensitivity and specificity, assay methodology, sample handling, timing of sample collection, concomitant medications, underlying disease, and the number of patients tested. For these reasons, comparison of the incidence of antibodies to canakinumab between the CAPS, SJIA, and gout flare clinical studies or with the incidence of antibodies to other products may be misleading.

No TRAPS, HIDS/MKD, FMF, SJIA, or AOSD patients treated with ILARIS doses of 150 mg and 300 mg over 16 weeks of treatment tested positive for anti-canakinumab antibodies.

6.3 Postmarketing Experience

The following adverse reactions have been identified during postapproval use of ILARIS. Because these reactions are reported voluntarily from a population of uncertain size, it is not always possible to reliably estimate their frequency or establish a causal relationship to drug exposure.

Skin and subcutaneous tissue disorders:

- Drug Reaction with Eosinophilia and Systemic Symptoms (DRESS) [see Warnings and Precautions (5.3)]

7 DRUG INTERACTIONS

Interactions between ILARIS and other medicinal products have not been investigated in formal studies.

7.1 TNF-Blocker and IL-1 Blocking Agent

An increased incidence of serious infections and an increased risk of neutropenia have been associated with administration of another IL-1 blocker in combination with TNF inhibitors in another patient population. Use of ILARIS with TNF inhibitors may also result in similar toxicities and is not recommended because this may increase the risk of serious infections [see Warnings and Precautions (5.1)].

The concomitant administration of ILARIS with other drugs that block IL-1 has not been studied. Based upon the potential for pharmacological interactions between ILARIS and a recombinant IL-1ra, concomitant administration of ILARIS and other agents that block IL-1 or its receptors is not recommended.

7.2 Immunization

No data are available on either the effects of live vaccination or the secondary transmission of infection by live vaccines in patients receiving ILARIS. Therefore, avoid administration of live vaccines concurrently with ILARIS. It is recommended that, if possible, pediatric and adult patients complete all immunizations in accordance with current immunization guidelines prior to initiating ILARIS therapy [see Warnings and Precautions (5.4)].

7.3 Cytochrome P450 Substrates

The formation of CYP450 enzymes is suppressed by increased levels of cytokines (e.g., IL-1) during chronic inflammation. Thus, it is expected that for a molecule that binds to IL-1, such as canakinumab, the formation of CYP450 enzymes could be normalized. This is clinically relevant for CYP450 substrates with a narrow therapeutic index, where the dose is individually adjusted (e.g., warfarin). Upon initiation of canakinumab, in patients being treated with these types of medicinal products, therapeutic monitoring of the effect or drug concentration should be performed, and the individual dose of the medicinal product may need to be adjusted as needed.

8 USE IN SPECIFIC POPULATIONS

8.1 Pregnancy

Risk Summary

Available human data from postmarketing experience and published case reports on ILARIS use in pregnant women are insufficient to identify a drug-associated risk of major birth defects, miscarriage, and adverse maternal or fetal outcomes. Canakinumab, like other monoclonal antibodies, is actively transported across the placenta mainly during the third trimester of pregnancy and may cause immunosuppression in the in utero exposed infant (see Clinical Considerations).

In an animal embryo-fetal development study with marmoset monkeys, there was no evidence of embryotoxicity or fetal malformations with subcutaneous administration of canakinumab during the period of organogenesis and later in gestation at doses that produced exposures approximately 11 times the exposure at the maximum recommended human dose (MRHD) and greater. Delays in fetal skeletal development were observed in marmoset monkeys following prenatal exposure to ILARIS at concentrations approximately 11 times the MRHD and greater. Similar delays in fetal skeletal development were observed in mice administered a murine analog of ILARIS during the period of organogenesis. Delays in skeletal ossification are changes from the expected ossification state in an otherwise normal structure/bone: these findings are generally reversible or transitory and not detrimental to postnatal survival (see Animal Data).

The estimated background risk of major birth defects and miscarriage for the indicated population(s) are unknown. In the U.S. general population, the estimated background risk of major birth defects and miscarriage in clinically recognized pregnancies is 2% to 4% and 15% to 20%, respectively.

Clinical Considerations

Fetal/Neonatal Adverse Reactions

Monoclonal antibodies are increasingly transported across the placenta as pregnancy progresses, with the largest amount transferred during the third trimester. Because IL-1 blockade may interfere with immune response to infections, risks and benefits should be considered prior to administering live vaccines to infants who were exposed to ILARIS in utero for at least 4 to 12 months following the mother’s last dose of ILARIS. The ideal time to avoid live vaccines in infants exposed to ILARIS in utero is unknown, as there are insufficient data regarding infant serum levels of canakinumab at birth and the duration of persistence of canakinumab in infant serum after birth is also unknown.

Data

Animal Data

In an embryo-fetal development study, pregnant marmoset monkeys received canakinumab from gestation days 25 to 109 at doses that produced exposures approximately 11 times that achieved with MRHD and greater (on a plasma area under the curve [AUC] basis with maternal subcutaneous doses of 15, 50, or 150 mg/kg twice weekly). ILARIS did not elicit any evidence of embryotoxicity or fetal malformations. There were increases in the incidence of incomplete ossification of the terminal caudal vertebra and misaligned and/or bipartite vertebra in fetuses at all dose levels when compared to concurrent controls suggestive of delay in skeletal development in the marmoset. Since ILARIS does not cross-react with mouse or rat IL-1β, pregnant mice were subcutaneously administered a murine analog of ILARIS at doses of 15, 50, or 150 mg/kg during the period of organogenesis on gestation days 6, 11, and 17. The incidence of incomplete ossification of the parietal and frontal skull bones of fetuses was increased in a dose-dependent manner at all dose levels tested.

8.2 Lactation

Risk Summary

There is no information regarding the presence of canakinumab in human milk or the effects on milk production. There are a small number of published case reports that do not establish an association between maternal canakinumab use during lactation and adverse effects on breastfed infants. Maternal IgG is known to be present in human milk. The effects of canakinumab in breast milk and possible systemic exposure in the breastfed infant are unknown. The developmental and health benefits of breastfeeding should be considered along with the mother’s clinical need for ILARIS and any potential adverse effects on the breastfed infant from ILARIS or from the underlying maternal condition.

8.4 Pediatric Use

The CAPS trials with ILARIS included a total of 23 pediatric patients with an age range from 4 years to 17 years (11 adolescents were treated subcutaneously with 150 mg, and 12 children were treated with 2 mg/kg based on body weight greater than or equal to 15 kg and less than or equal to 40 kg). The majority of patients achieved improvement in clinical symptoms and objective markers of inflammation (e.g., Serum Amyloid A [SAA] and C-Reactive Protein). Overall, the efficacy and safety of ILARIS in pediatric and adult patients were comparable. Infections of the upper respiratory tract were the most frequently reported infection. The safety and effectiveness of ILARIS in CAPS patients less than 4 years of age has not been established [see Adverse Reactions (6.1), Clinical Pharmacology (12.3), and Clinical Studies (14.1)].

The safety and effectiveness of ILARIS in SJIA patients less than 2 years of age have not been established [see Adverse Reactions (6.1), Clinical Pharmacology (12.3), and Clinical Studies (14.3)].

The TRAPS, HIDS/MKD, and FMF trial included a total of 102 pediatric patients (TRAPS, HIDS/MKD and FMF patients) with an age range from 2 to 17 years who received ILARIS. Overall, there were no clinically meaningful differences in the efficacy, safety and tolerability profile of ILARIS in pediatric patients compared to the overall TRAPS, HIDS/MKD, and FMF populations (comprised of adult and pediatric patients, N = 169). The majority of pediatric patients achieved improvement in clinical symptoms and objective markers of inflammation [see Adverse Reactions (6.1), Clinical Pharmacology (12.3), and Clinical Studies (14.2)].

The safety and effectiveness of ILARIS for the treatment of gout flares in the pediatric population have not been established.

Because IL-1 blockade may interfere with immune response to infections, it is recommended that prior to initiation of therapy with ILARIS, pediatric patients receive all recommended vaccinations. Avoid use of live virus vaccines concurrently with ILARIS treatment in pediatric patients or in infants exposed in utero following maternal administration [see Warnings and Precautions (5.4) and Use in Specific Populations (8.1)].

8.5 Geriatric Use

Clinical studies of ILARIS in patients with CAPS, TRAPS, HIDS/MKD, FMF and Still’s disease, did not include sufficient numbers of patients 65 years and older to determine whether they respond differently from younger patients.

In the clinical studies for gout flares, of the total number of ILARIS- treated patients (n=491), 85 (17.3 %) were 65 years of age and older, while 16 (3.3 %) were 75 years of age and older [see Clinical Studies (14.4)]. Overall, the efficacy profile of ILARIS in patients with gout flares was comparable between the age group of patients less than 65 years of age, and of patients 65 to 75 years of age. The studies did not include sufficient numbers of patients 75 years and older to determine whether they respond differently from younger patients. No new safety findings were observed in patients across these age groups [see Adverse Reactions (6.1)].

8.6 Renal Impairment

No formal studies have been conducted to examine the pharmacokinetics of ILARIS administered subcutaneously in patients with renal impairment.

8.7 Hepatic Impairment

No formal studies have been conducted to examine the pharmacokinetics of ILARIS administered subcutaneously in patients with hepatic impairment.

10 OVERDOSAGE

No confirmed case of overdose has been reported. In the case of overdose, it is recommended that the subject be monitored for any signs and symptoms of adverse reactions or effects, and appropriate symptomatic treatment be instituted immediately.

11 DESCRIPTION

Canakinumab is a recombinant, human anti-human-IL-1β monoclonal antibody that belongs to the IgG1/κ isotype subclass. It is expressed in a murine Sp2/0-Ag14 cell line and comprised of two 447- (or 448-) residue heavy chains and two 214-residue light chains, with a molecular mass of 145157 Daltons when deglycosylated. Both heavy chains of canakinumab contain oligosaccharide chains linked to the protein backbone at asparagine 298 (Asn 298).

The biological activity of canakinumab is measured by comparing its inhibition of IL-1β-dependent expression of the reporter gene luciferase to that of a canakinumab internal reference standard, using a stably transfected cell line.

ILARIS Injection

ILARIS (canakinumab) Injection is supplied as a sterile, preservative-free, clear to opalescent, colorless to slightly brownish-yellow solution for subcutaneous injection in a single-dose, glass vial with coated stopper and aluminum flip-off cap. Each vial delivers 1 mL containing 150 mg canakinumab, L-histidine (2.1 mg), L-histidine HCl monohydrate (1.3 mg), mannitol (49.2 mg), polysorbate 80 (0.4 mg), and Sterile Water for Injection.

12 CLINICAL PHARMACOLOGY

12.1 Mechanism of Action

Canakinumab is a human monoclonal anti-human IL-1β antibody of the IgG1/κ isotype. Canakinumab binds to human IL-1β and neutralizes its activity by blocking its interaction with IL-1 receptors, but it does not bind IL-1α or IL-1 receptor antagonist (IL-1ra).

CAPS refer to rare genetic syndromes generally caused by mutations in the NLRP-3 [nucleotide-binding domain, leucine rich family (NLR), pyrin domain containing 3] gene (also known as Cold-Induced Autoinflammatory Syndrome-1 [CIAS1]). CAPS disorders are inherited in an autosomal dominant pattern with male and female offspring equally affected. Features common to all disorders include fever, urticaria-like rash, arthralgia, myalgia, fatigue, and conjunctivitis.

The NLRP3 protein is an important component of the inflammasome and regulates the protease caspase-1 and controls the activation of IL-1β. Mutations in NLRP3 result in an overactive inflammasome resulting in excessive release of activated IL-1β that drives inflammation. Still’s disease is a severe autoinflammatory disease, driven by innate immunity by means of proinflammatory cytokines such as IL-1β.

Gout flares are characterized by activation of resident macrophages and infiltrating neutrophils in the joint, and concomitant overproduction of IL-1β resulting in an acute painful inflammatory response. IL-1β production by macrophages is triggered by uric acid (monosodium urate monohydrate) crystals in the joint and surrounding tissue through activation of the NLRP3 inflammasome complex.

12.2 Pharmacodynamics

C-reactive protein and Serum Amyloid A (SAA) are indicators of inflammatory disease activity that are elevated in patients with CAPS and gout flares. Elevated SAA has been associated with the development of systemic amyloidosis in patients with CAPS. Following ILARIS treatment, CRP, and SAA levels normalize within 8 days.

In patients with gout flares, CRP and SAA were rapidly reduced following ILARIS treatment. Reductions in CRP and SAA were sustained throughout the 24-week observation period. Improvement in pharmacodynamic markers may not be representative of clinical response.

In SJIA the median percent reduction in CRP from baseline to Day 15 was 91%. Improvement in pharmacodynamic markers may not be representative of clinical response.

12.3 Pharmacokinetics

The pharmacokinetic properties of canakinumab are typical for an IgG-type antibody and are comparable in different diseases but influenced by body weight.

Absorption

The peak serum canakinumab concentration (Cmax) of 16 ± 3.5 mcg/mL occurred approximately 7 days after subcutaneous administration of a single, 150 mg dose subcutaneously to adult CAPS patients. The mean terminal half-life was 26 days. The absolute bioavailability of subcutaneous canakinumab was estimated to be 66%. Exposure parameters (such as AUC and Cmax) increased in proportion to dose over the dose range of 0.30 to 10 mg/kg given as intravenous infusion or from 150 to 300 mg as subcutaneous injection.

Distribution

Canakinumab binds to serum IL-1β. Canakinumab volume of distribution (Vss) varied according to body weight and was estimated to be 6.01 liters in a typical CAPS patient weighing 70 kg, 3.2 liters in a SJIA patient weighing 33 kg, and 6.34 liters for a Periodic Fever Syndrome (TRAPS, HIDS/MKD, FMF) patient weighing 70 kg and 7.9 liters in a typical patient with gout flares of body weight 93 kg. The expected accumulation ratio was 1.3-fold for CAPS patients, 1.6-fold for SJIA patients, and 1.1-fold for patients with gout flares following 6 months of subcutaneous dosing of 150 mg ILARIS every 8 weeks, 4 mg/kg every 4 weeks, and 150 mg every 12 weeks, respectively.

Elimination

Clearance (CL) of canakinumab varied according to body weight and was estimated to be 0.174 L/day in a typical CAPS patient weighing 70 kg, 0.11 L/day in an SJIA patient weighing 33 kg, and 0.17 L/day in a Periodic Fever Syndrome (TRAPS, HIDS/MKD, FMF) patient weighing 70 kg and 0.23 L/day in a typical patient with gout flares of body weight 93 kg. There was no indication of accelerated clearance or time-dependent change in the pharmacokinetic properties of canakinumab following repeated administration. No gender- or age-related pharmacokinetic differences were observed after correction for body weight.

Specific Populations

Pediatric Patients

Pharmacokinetic properties are similar in Periodic Fever Syndromes (CAPS, TRAPS, HIDS/MKD, FMF) and SJIA pediatric populations. In patients less than 2 years of age (n = 7), the exposure of canakinumab were comparable to older age groups with the same weight-based dose.

In CAPS patients, peak concentrations of canakinumab occurred between 2 to 7 days following single subcutaneous administration of ILARIS 150 mg or 2 mg/kg in pediatric patients. The terminal half-life ranged from 22.9 to 25.7 days, similar to the pharmacokinetic properties observed in adults.

In SJIA, exposure parameters (such as AUC and Cmax) were comparable across age groups from 2 years of age and above following subcutaneous administration of canakinumab 4 mg/kg every 4 weeks. Across the indications, SJIA and AOSD, the pharmacokinetics of canakinumab are similar.

In TRAPS, HIDS/MKD, and FMF exposure parameter trough concentrations were comparable across age groups from 2 to less than 20 years following subcutaneous administration of canakinumab 2 mg/kg every 4 weeks.

13 NONCLINICAL TOXICOLOGY

13.1 Carcinogenesis, Mutagenesis, Impairment of Fertility

Long-term animal studies have not been performed to evaluate the carcinogenic potential of canakinumab.

As canakinumab does not cross-react with rodent IL-1β, male and female fertility were evaluated in a mouse model using a murine analog of canakinumab. Male mice were treated weekly beginning 4 weeks prior to mating and continuing through 3 weeks after mating. Female mice were treated weekly for 2 weeks prior to mating through gestation day 3 or 4. The murine analog of canakinumab did not alter either male or female fertility parameters at subcutaneous doses up to 150 mg/kg.

14 CLINICAL STUDIES

14.1 Treatment of CAPS

The efficacy and safety of ILARIS for the treatment of CAPS was demonstrated in CAPS Study (NCT00465985), a 3-part trial in patients 9 to 74 years of age with the MWS phenotype of CAPS. Throughout the trial, patients weighing more than 40 kg received ILARIS 150 mg and patients weighing 15 to 40 kg received 2 mg/kg. Part 1 was an 8-week open-label, single-dose period where all patients received ILARIS. Patients who achieved a complete clinical response and did not relapse by Week 8 were randomized into Part 2, a 24-week randomized, double-blind, placebo-controlled withdrawal period. Patients who completed Part 2 or experienced a disease flare entered Part 3, a 16-week open-label active treatment phase. A complete response was defined as ratings of minimal or better for physician’s assessment of disease activity (PHY) and assessment of skin disease (SKD) and had serum levels of C-Reactive Protein (CRP) and Serum Amyloid A (SAA) less than 10 mg/L. A disease flare was defined as a CRP and/or SAA values greater than 30 mg/L and either a score of mild or worse for PHY or a score of minimal or worse for PHY and SKD.

In Part 1, a complete clinical response was observed in 71% of patients one week following initiation of treatment and in 97% of patients by Week 8 (see Table 4 and Figure 1). In the randomized withdrawal period, a total of 81% of the patients randomized to placebo flared as compared to none (0%) of the patients randomized to ILARIS. The 95% confidence interval for treatment difference in the proportion of flares was 53% to 96%. At the end of Part 2, all 15 patients treated with ILARIS had absent or minimal disease activity and skin disease (see Table 4).

In a second trial (NCT00465985), patients 4 to 74 years of age with both MWS and FCAS phenotypes of CAPS were treated in an open-label manner. Treatment with ILARIS resulted in clinically significant improvement of signs and symptoms and in normalization of high CRP and SAA in a majority of patients within 1 week.

Table 4: Physician’s Global Assessment of Auto Inflammatory Disease Activity and Assessment of Skin Disease: Frequency Table and Treatment Comparison in Part 2 (Using LOCF, ITT Population)
 |  | ILARIS N = 15 |  | Placebo N = 16
 | Baseline | Start of Part 2 (Week 8) | End of Part 2 |  | Start of Part 2 (Week 8) | End of Part 2
Physician's Global Assessment of Auto Inflammatory Disease Activity – n (%)
Absent | 0/31 (0) | 9/15 (60) | 8/15 (53) | 8/16 (50) |  | 0/16 (0)
Minimal | 1/31 (3) | 4/15 (27) | 7/15 (47) | 8/16 (50) |  | 4/16 (25)
Mild | 7/31 (23) | 2/15 (13) | 0/15 (0) | 0/16 (0) |  | 8/16 (50)
Moderate | 19/31 (61) | 0/15 (0) | 0/15 (0) | 0/16 (0) |  | 4/16 (25)
Severe | 4/31 (13) | 0/15 (0) | 0/15 (0) | 0/16 (0) |  | 0/16 (0)
Assessment of skin disease – n (%)
Absent | 3/31 (10) | 13/15 (87) | 14/15 (93) |  | 13/16 (81) | 5/16 (31)
Minimal | 6/31 (19) | 2/15 (13) | 1/15 (7) |  | 3/16 (19) | 3/16 (19)
Mild | 9/31 (29) | 0/15 (0) | 0/15 (0) |  | 0/16 (0) | 5/16 (31)
Moderate | 12/31 (39) | 0/15 (0) | 0/15 (0) |  | 0/16 (0) | 3/16 (19)
Severe | 1/32 (3) | 0/15 (0) | 0/15 (0) |  | 0/16 (0) | 0/16 (0)

Markers of inflammation CRP and SAA normalized within 8 days of treatment in the majority of patients. Normal mean CRP (Figure 1) and SAA values were sustained throughout CAPS Study 1 in patients continuously treated with canakinumab. After withdrawal of canakinumab in Part 2, CRP (Figure 1) and SAA values again returned to abnormal values and subsequently normalized after reintroduction of canakinumab in Part 3. The pattern of normalization of CRP and SAA was similar.

Figure 1. Mean C-Reactive Protein Levels at the End of Parts 1, 2, and 3 of CAPS Study 1

14.2 Treatment of Periodic Fever Syndromes: TRAPS, HIDS/MKD, and FMF

The efficacy and safety of ILARIS for the treatment of TRAPS, HIDS/MKD, and FMF was demonstrated in a 4-Part study (TRAPS, HIDS/MKD, and FMF Study 1) (NCT02059291) consisting of three separate, disease cohorts (TRAPS, HIDS/MKD, and FMF) which enrolled 185 patients aged greater than 28 days. Patients in each cohort entered a 12-week screening period (Part 1) during which they were evaluated for the onset of disease flare. Patients aged 2 to 76 years were then randomized at flare onset into a 16-week double-blind, placebo-controlled treatment period (Part 2) where they received either 150 mg ILARIS (2 mg/kg for patients weighing less than or equal to 40 kg) subcutaneously or placebo every 4 weeks. Part 3 and Part 4 of this study are ongoing.

Randomized patients in Part 2 treated with ILARIS whose disease flare did not resolve, or who had persistent disease activity from Day 8 up to Day 14 (Physician’s Global Assessment [PGA] greater than or equal to 2 or C-reactive Protein [CRP] greater than 10 mg/L and no reduction by at least 40% from baseline) received an additional dose of 150 mg (or 2 mg/kg for patients weighing less than or equal to 40 kg). Patients treated with ILARIS whose disease flare did not resolve, or who had persistent disease activity from Day 15 up to Day 28 (PGA greater than or equal to 2 or CRP greater than 10 mg/L and no reduction by at least 70% from baseline), also received an additional dose of 150 mg (or 2 mg/kg for patients weighing less than or equal to 40 kg). On or after Day 29, patients treated with ILARIS in Part 2 with PGA greater than or equal to 2 and CRP greater than or equal to 30 mg/L were also up-titrated. All up-titrated patients remained at the increased dose of 300 mg (or 4 mg/kg for patients weighing less than or equal to 40 kg) every 4 weeks.

The primary efficacy endpoint of the randomized, 16-week treatment period (Part 2) was the proportion of complete responders within each cohort as defined by patients who had resolution of their index disease flare at Day 15 and did not experience a new disease flare during the remainder of the 16-week treatment period. Resolution of the index disease flare (initial flare at the time of the randomization) was defined at the Day 15 visit as a PGA Disease Activity score less than 2 (“minimal or no disease”) and C-reactive Protein (CRP) within normal range (less than or equal to 10 mg/L) or reduction greater than or equal to 70% from baseline. The key signs and symptoms assessed in the PGA for each condition were the following: TRAPS: abdominal pain, skin rash, musculoskeletal pain, eye manifestations; HIDS/MKD: abdominal pain; lymphadenopathy, aphthous ulcers; FMF: abdominal pain, skin rash, chest pain, arthralgia/arthritis. A new flare was defined as a PGA score greater than or equal to 2 (“mild, moderate, or severe disease”) and CRP greater to or equal than 30 mg/L. In the 16-week treatment period (Part 2), patients who needed dose escalation, who crossed over from placebo to ILARIS, or who discontinued from the study due to any reason prior to Week 16 were considered as non-responders.

Patients randomized in the TRAPS cohort (N = 46) were aged 2 to 76 years (median age at baseline: 15.5 years) and of this population, 57.8% did not have fever at baseline. Randomized TRAPS patients were those with chronic or recurrent disease activity defined as 6 flares per year (median number of flares per year: 9.0) with PGA greater than or equal to 2 and CRP greater than 10 mg/L (median CRP at baseline: 112.5 mg/L). In the TRAPS cohort, 11/22 (50.0%) patients randomized to ILARIS 150 mg every 4 weeks received up-titration to 300 mg every 4 weeks during the 16-week treatment period, while 21/24 (87.5%) patients randomized to placebo crossed over to ILARIS.

Patients randomized in the HIDS/MKD cohort (N = 72) were aged 2 to 47 years (median age at baseline: 11.0 years) and of this population, 41.7% did not have fever at baseline. Randomized HIDS/MKD patients were those with a confirmed diagnosis of HIDS according to known genetic MVK/enzymatic (MKD) findings, and documented prior history of greater than or equal to 3 febrile acute flares within a 6-month period (median number of flares per year: 12.0) when not receiving prophylactic treatment and during the study, had active HIDS flares defined as PGA greater than or equal to 2 and CRP greater than 10 mg/L (median CRP at baseline: 113.5 mg/L). In the HIDS/MKD cohort, 19/37 (51.4%) patients randomized to ILARIS 150 mg every 4 weeks received up-titration to 300 mg every 4 weeks during the 16-week treatment period, while 31/35 (88.6%) patients randomized to placebo crossed over to ILARIS.

Patients randomized in the FMF cohort (N = 63) were aged 2 to 69 years (median age at baseline: 18.0 years) and of this population, 76.2% did not have fever at baseline. Randomized FMF patients were those with documented active disease despite colchicine therapy or documented intolerance to effective doses of colchicine. Patients had active disease defined as at least one flare per month (median number of flares per year: 18.0) and CRP greater than 10 mg/L (median CRP at baseline: 94.0 mg/L). Patients were allowed to continue their stable dose of colchicine without change. Of the 63 randomized patients, 55 (87.3%) were taking concomitant colchicine therapy on or after randomization. In the FMF cohort, 10/31 (32.3%) patients randomized to ILARIS 150 mg every 4 weeks received up-titration to 300 mg every 4 weeks during the 16-week treatment period, while 27/32 (84.4%) patients randomized to placebo crossed over to ILARIS.

For the primary efficacy endpoint, ILARIS was superior to placebo in the proportion of TRAPS, HIDS/MKD, and FMF patients who resolved their index disease flare at Day 15 and had no new flare over the 16 weeks of treatment from the time of the resolution of the index flare (see Table 5).

Table 5: Proportion of TRAPS, HIDS/MKD, and FMF Patients Who Achieved a Complete Response (Resolution of Index Flare by Day 15 and Maintained Through Week 16)
 | ILARIS 150 mg | Placebo | Treatment comparison
Cohort | n/N (%) | n/N (%) | Odds ratio 95% CI | p-value
TRAPS | 10/22 (45.5%) | 2/24 (8.3%) | 9.17 (1.51, 94.61) | 0.005
HIDS/MKD | 13/37 (35.1%) | 2/35 (5.7%) | 8.94 (1.72, 86.41) | 0.002
FMF | 19/31 (61.3%) | 2/32 (6.3%) | 23.75 (4.38, 227.53) | <0.0001
Abbreviation: CI, confidence interval.
n = number of patients with the response.
N = number of patients evaluated for that response in each cohort.

At Day 15, a higher proportion of ILARIS-treated patients compared to placebo-treated patients experienced resolution of their index flare in all disease cohorts (see Table 6).

Table 6: Resolution of Index Flare (Full Analysis Set)
 | Resolution at Day 15*
 | ILARIS 150 mg every 4 weeks | Placebo
Variable | n/N (%) | n/N (%)
TRAPS | 14/22 (63.6%) | 5/24 (20.8%)
HIDS/MKD | 24/37 (64.9%) | 13/35 (37.1%)
FMF | 25/31 (80.7%) | 10/32 (31.3%)
n = number of patients with the response.
N = number of patients evaluated for that response in each cohort.
*Resolution of index disease flare (PGA less than 2 and CRP less than or equal to 10 mg/L or reduction greater than or equal to 70% from baseline).

There was supportive evidence of efficacy for ILARIS at Day 15, as compared to placebo, for the components of the primary endpoint, CRP and PGA Disease Activity score, as well as for the secondary endpoint SAA level (see Table 7).

Table 7: Proportion of TRAPS, HIDS/MKD, and FMF Patients Achieving PGA Less Than 2, CRP Less Than or Equal to 10 mg/L and SAA Less Than or Equal to 10 mg/L at Day 15*
 | TRAPS |  |  | HIDS/MKD |  |  | FMF
Variable | ILARIS 150 mg | Placebo | Treatment comparison | ILARIS 150 mg | Placebo | Treatment comparison | ILARIS 150 mg | Placebo | Treatment comparison
 | n/N (%) | n/N (%) | Odds ratio 95% CI | n/N (%) | n/N (%) | Odds ratio 95% CI | n/N (%) | n/N (%) | Odds ratio 95% CI
PGA less than 2 | 14/22 (63.6%) | 8/24 (33.3%) | 4.06 (1.12, 14.72) | 26/37 (70.3%) | 14/35 (40.0%) | 3.42 (1.28, 9.16) | 27/31 (87.1%) | 13/32 (40.6%) | 10.07 (2.78, 36.49)
CRP less than or equal to 10 mg/L | 13/22 (59.1%) | 8/24 (33.3%) | 3.88 (1.05, 14.26) | 25/37 (67.6%) | 9/35 (25.7%) | 6.05 (2.14, 17.12) | 28/31 (90.3%) | 9/32 (28.1%) | 22.51 (5.41, 93.62)
SAA less than or equal to 10 mg/L | 7/22 (31.8%) | 2/24 (8.3%) | 5.06 (0.92, 27.91) | 10/37 (27.0%) | 4/35 (11.4%) | 2.94 (0.82, 10.53) | 13/31 (41.9%) | 5/32 (15.6%) | 3.73 (1.11, 12.52)
Abbreviation: CI: confidence interval.
n = number of patients with the response.
N = number of patients evaluated for that response in each cohort.
*ILARIS-treated patients who up-titrated or discontinued prior to Day 15 and placebo-treated patients who switched over to ILARIS or discontinued prior to Day 15 were classified as nonresponders.

14.3 Treatment of Still’s Disease: AOSD and SJIA

SJIA

The efficacy of ILARIS for the treatment of active SJIA was assessed in 2 Phase 3 studies (SJIA Study 1 and SJIA Study 2). Patients enrolled were aged 2 to less than 20 years (mean age at baseline: 8.5 years) with a confirmed diagnosis of SJIA at least 2 months before enrollment (mean disease duration at baseline: 3.5 years). Patients had active disease defined as greater than or equal to 2 joints with active arthritis (mean number of active joints at baseline: 15.4), documented spiking, intermittent fever (body temperature greater than 38°C) for at least 1 day within 1 week before study drug administration, and CRP greater than 30 mg/L (normal range less than 10 mg/L) (mean CRP at baseline: 200.5 mg/L). Patients were allowed to continue their stable dose of methotrexate, corticosteroids, and/or NSAIDs without change, except for tapering of the corticosteroid dose as per study design in SJIA Study 2 (see below).

SJIA Study 1 (NCT00886769) was a randomized, double-blind, placebo-controlled, single-dose 4-week study assessing the short-term efficacy of ILARIS in 84 patients randomized to receive a single subcutaneous dose of 4 mg/kg ILARIS or placebo (43 patients received ILARIS and 41 patients received placebo). The primary objective of this study was to demonstrate the superiority of ILARIS versus placebo in the proportion of patients who achieved at least 30% improvement in an adapted pediatric American College of Rheumatology (ACR) response criterion which included both the pediatric ACR core set (ACR30 response) and absence of fever (temperature less than or equal to 38°C in the preceding 7 days) at Day 15.

Pediatric ACR responses are defined by achieving levels of percentage improvement (30%, 50%, and 70%) from baseline in at least 3 of the 6 core outcome variables, with worsening of greater than or equal to 30% in no more than one of the remaining variables. Core outcome variables included a physician global assessment of disease activity, parent or patient global assessment of well-being, number of joints with active arthritis, number of joints with limited range of motion, CRP, and functional ability (Childhood Health Assessment Questionnaire-CHAQ).

Percentages of patients by pediatric ACR response are presented in Table 8.

Table 8: Pediatric ACR Response at Days 15 and 29
 | Day 15 |  |  | Day 29
 | ILARIS | Placebo | Weighted Difference^1 (95% CI)^2 | ILARIS | Placebo | Weighted difference^1 (95% CI)^2
 | N = 43 | N = 41 |  | N = 43 | N = 41
ACR30 | 84% | 10% | 70% (56%, 84%) | 81% | 10% | 70% (56%, 84%)
ACR50 | 67% | 5% | 65% (50%, 80%) | 79% | 5% | 76% (63%, 88%)
ACR70 | 60% | 2% | 64% (49%, 79%) | 67% | 2% | 67% (52%, 81%)
^1Weighted difference is the difference between the ILARIS and placebo response rates, adjusted for the stratification factors (number of active joints, previous response to anakinra, and level of oral corticosteroid use).
^2CI = confidence interval for the weighted difference.
N = Number of patients.

Results for the components of the pediatric ACR core set were consistent with the overall ACR response results, for systemic and arthritic components, including the reduction in the total number of active joints and joints with limited range of motion. Among the patients who returned for a Day 15 visit, the mean change in patient pain score (0 to 100 mm visual analogue scale) was -50.0 mm on ILARIS (N = 43), as compared to +4.5 mm on placebo (N = 25). The mean change in pain score among ILARIS-treated patients was consistent through Day 29. All patients treated with ILARIS had no fever at Day 3 compared to 87% of patients treated with placebo.

SJIA Study 2 (NCT00889863) was a randomized, double-blind, placebo-controlled, withdrawal study of flare prevention by ILARIS in patients with active SJIA. Flare was defined by worsening of greater than or equal to 30% in at least 3 of the 6 core Pediatric ACR response variables combined with improvement of greater than or equal to 30% in no more than 1 of the 6 variables, or reappearance of fever not due to infection for at least 2 consecutive days. The study consisted of 2 major parts: 177 patients were enrolled in the study and received 4 mg/kg ILARIS subcutaneously every 4 weeks in Part I and 100 of these patients continued into Part II to receive either ILARIS 4 mg/kg or placebo subcutaneously every 4 weeks.

Corticosteroid Dose Tapering

Of the total 128 patients taking corticosteroids who entered the open-label portion of Study 2, 92 attempted corticosteroid tapering. Fifty-seven (62%) of the 92 patients who attempted to taper were able to successfully taper their corticosteroid dose and 42 (46%) discontinued corticosteroids.

Time to Flare

Part II was a randomized withdrawal design to demonstrate that the time to flare was longer with ILARIS than with placebo. Follow-up stopped when 37 events had been observed resulting in patients being followed for different lengths of time. The probability of experiencing a flare over time in Part II was statistically lower for the ILARIS treatment group than for the placebo group (Figure 2). This corresponded to a 64% relative reduction in the risk of flare for patients in the ILARIS group as compared to those in the placebo group (hazard ratio of 0.36; 95% CI: 0.17 to 0.75).

Figure 2. Kaplan-Meier Estimates of the Probability to Stay Flare-Free in Part II of SJIA Study 2 by Treatment (ILARIS (ACZ885) and Placebo groups)

Very few patients were followed for more than 48 weeks.

AOSD

The efficacy of ILARIS in adults with AOSD is based on the pharmacokinetic exposure and extrapolation of the established efficacy of ILARIS in SJIA patients. Efficacy of ILARIS was also assessed in a randomized, double-blind, placebo-controlled study that enrolled 36 patients (22 to 70 years old) diagnosed with AOSD. The efficacy data were generally consistent with the results of a pooled efficacy analysis of SJIA patients.

14.4 Treatment of Gout Flares

The efficacy of ILARIS was demonstrated in two 12-week, randomized, double-blind, active-controlled studies in patients with gout flares for whom NSAIDs and/or colchicine were contraindicated, not tolerated or ineffective, and who had experienced at least three gout flares in the previous year (Studies 1 and 2). The studies continued in 1) two 12-week, double-blind, active-controlled extensions, followed by 2) two open-label extensions and continued 3) in a third open-label extension (combined for both studies) up to a maximum of 36 months where all patients were treated with ILARIS upon a new flare.

In Study 1 (NCT01029652), patients were randomized to receive ILARIS 150 mg subcutaneous (N = 115) or triamcinolone acetonide 40 mg intramuscular (N = 115) at baseline and thereafter treated upon a new flare. Two patients randomized to canakinumab were not included in the analysis as they did not receive any study medication. In Study 2 (NCT01080131), patients were randomized to receive ILARIS 150 mg subcutaneous (N =112) or triamcinolone acetonide 40 mg intramuscular (N =114) at baseline and thereafter treated upon a new flare.

In Studies 1 and 2, over 85% of patients had at least one co-morbidity, including hypertension (60%), obesity (53%), diabetes (15%), and ischemic heart disease (12%). Twenty-five percent of patients had chronic kidney disease (stage ≥ 3), based on eGFR. Concomitant treatment with allopurinol or other uric acid lowering therapies was reported by 42% of patients at entry.

The majority of patients (73%) reported between 3-6 flares in the year prior to study entry and the remainder reported seven or more flares. Approximately one-third of the patients enrolled [76 in the ILARIS group (33.5%) and 84 in the triamcinolone acetonide (36.7%) group] had documented inability (intolerance, contraindication or lack of response) to use both, NSAIDs and colchicine. The remainder had intolerance, contraindication or lack of response to either NSAIDs or colchicine.

In both studies, the co-primary endpoints were: (i) patient’s assessment of gout flare pain intensity at the most affected joint at 72 hours post-dose measured on a 0-100 mm visual analogue scale (VAS) and (ii) the time to first new gout flare. The studies aimed to determine whether ILARIS 150 mg would be superior to triamcinolone acetonide 40 mg.

Study 3 (NCT01356602), an additional 12-week, randomized, double-blind, active-controlled study, enrolled 397 patients with ILARIS 150 mg subcutaneous (Pre-Filled Syringe (PFS), N=133, Lyophilizate (LYO), N=132) or triamcinolone acetonide 40 mg intramuscular (N=132). Eight patients (2 ILARIS PFS, 3 ILARIS LYO, 3 triamcinolone) were not included for efficacy assessment as they did not receive study medication. Pain intensity at the most affected joint, assessed on a 0-100 mm VAS at 72-hours post-dose was the primary endpoint, and time to first new gout flare was a secondary endpoint. Approximately 44% of patients (45.9% ILARIS PFS group, 47.4%, ILARIS LYO group and 40.6% in the triamcinolone acetonide group) were unable to use NSAIDs and colchicine (due to contraindications, intolerance, or inadequate response) in this study.

Analyses of both endpoints were conducted for Studies 1, 2, and 3 for the subpopulation of patients unable to use NSAIDs and colchicine (due to contraindications, intolerance, or inadequate response) and overall population of patients unable to use NSAIDs and/or colchicine.

Efficacy on Pain

In all studies (Study 1, 2, and 3), pain intensity of the most affected joint (0-100 mm VAS) at 72 hours post-dose was consistently lower for patients treated with ILARIS compared with triamcinolone acetonide in the subpopulation of patients unable to use NSAIDs and colchicine as shown in Table 9, and Figure 3 (Study 3). This benefit of ILARIS on pain intensity was comparable to the overall patient populations i.e., patients unable to use NSAIDs and/or colchicine in all three studies (see Table 9).

Table 9: Pain Intensity of the Most Affected Joint at 72-h post treatment
Study | Population | ILARIS 150 mg |  | Triamcinolone acetonide 40 mg |  | Difference (95% CI)* in Pain Intensity 72 Hours Post-dose VAS (0-100 mm): ILARIS vs. Triamcinolone acetonide
 |  | N | Mean (SE)* | N | Mean (SE)*
Study 1 | Patients unable to use NSAIDs and colchicine | 22 | 21.4 (6.05) | 37 | 38.4 (4.65) | -17.0 mm (-32.3, -1.6)
 | Patients unable to use NSAIDs and/or colchicine | 113 | 27.9 (2.42) | 115 | 39.7 (2.40) | -11.8 mm (-18.5, -5.1)
Study 2 | Patients unable to use NSAIDs and colchicine | 53 | 24.1 (3.32) | 44 | 33.1 (3.65) | -9.1 mm (-18.9, 0.8)
 | Patients unable to use NSAIDs and/or colchicine | 112 | 21.9 (2.31) | 114 | 31.7 (2.29) | -9.8 mm (-16.2, -3.4)
Study 3 | Patients unable to use NSAIDs and colchicine | 62 | 20.8 (3.11) | 51 | 40.3 (3.42) | -19.5 mm (-28.6, -10.3)
 |  | 60# | 18.5 (3.16) |  |  | -21.8 mm (-31.0, -12.6)
 | Patients unable to use NSAIDs and/or colchicine | 129 | 19.7 (2.05) | 129 | 32.4 (2.05) | -12.7 mm (-18.4, -7.0)
 |  | 131# | 17.0 (2.04) |  |  | -15.4 mm (-21.1, -9.8)
Abbreviation: CI = confidence interval; SE=Standard Error
#Prefilled Syringe (PFS) formulation.
*Adjusted mean, standard error for mean and difference between treatment groups are estimated based on analysis of covariance (ANCOVA) model with treatment, baseline VAS score and baseline BMI as covariates. For Study 3, the use of urate lowering therapy (Yes/No) at baseline is also included in the model as additional covariate.
N = number of patients randomized and received at least one dose of study treatment.

Figure 3. Pain Intensity Over Time in the Subpopulation of Patients Unable to Use NSAIDs and Colchicine (Study 3, ILARIS (ACZ885) 150mg)

Time to New Flare

In the subpopulation of patients in Studies 1, 2 and 3 unable to use NSAIDs and colchicine, time to new flare over 12 weeks from randomization showed a reduction in the risk of a new flare when treated with ILARIS compared with triamcinolone acetonide 40 mg (see Table 10).

This risk reduction for a new flare after ILARIS treatment versus triamcinolone acetonide was comparable to the overall patient population over 12 weeks in all 3 studies (see Table 10).

Table 10: Time to New Flare Over the 12 Weeks From Randomization
Study | Population | ILARIS 150 mg |  | Triamcinolone acetonide 40 mg |  | Risk reduction for a new flare ILARIS vs. Triamcinolone acetonide Hazard ratio# (95% CI)
 |  | N | Flare rate*(n) | N | Flare rate*(n)
Study 1 | Patients unable to use NSAIDs and colchicine | 22 | 14% (3) | 38 | 46% (17) | 75% 0.25 (0.07, 0.85)
 | Patients unable to use NSAIDs and/or colchicine | 113 | 19% (21) | 115 | 37% (40) | 55 % 0.45 (0.26 to 0.76)
Study 2 | Patients unable to use NSAIDs and colchicine | 54 | 16% (8) | 46 | 43% (19) | 72% 0.28 (0.12, 0.65)
 | Patients unable to use NSAIDs and/or colchicine | 112 | 14% (15) | 114 | 38% (42) | 68% 0.32 (0.18 to 0.58)
Study 3 | Patients unable to use NSAIDs and colchicine | 62 | 10% (6) | 51 | 32% (15) | 71% 0.29 (0.11, 0.74)
 |  | 60# | 3% (2) |  |  | 91% 0.09 (0.02, 0.41)
 | Patients unable to use NSAIDs and/or colchicine | 129 | 10% (12) | 129 | 44% (52) | 82% 0.18 (0.10, 0.34)
 |  | 131# | 9% (12) |  |  | 83% 0.17 (0.09, 0.33)
Abbreviation: CI = confidence interval.
#Prefilled Syringe (PFS) formulation.
* Flare rates up to 12 weeks are estimated using Kaplan-Meier method; n = number of patients with new flares. The risk reduction and hazard ratio between treatment groups are estimated using Cox proportional hazard (Cox-PH) model with treatment and baseline BMI as covariates. For study 3, the use of urate lowering therapy (Yes/No) at baseline is also included in the model as additional covariate.
N = number of patients randomized and received at least one dose of study treatment.

16 HOW SUPPLIED/STORAGE AND HANDLING

How Supplied

ILARIS Injection (Solution)

Carton of 1 vial NDC 0078-0734-61

Each single-dose vial of ILARIS (canakinumab) Injection delivers 150 mg/mL sterile, preservative-free, clear to slightly opalescent, colorless to a slight brownish to yellow solution.

Storage and Handling The unopened vial must be stored refrigerated at 2°C to 8°C (36°F to 46°F). Do not freeze. Store in the original carton to protect from light. Do not use beyond the date stamped on the label. ILARIS does not contain preservatives. Discard any unused portions of ILARIS or waste material in accordance with local requirements.

Keep this and all drugs out of the reach of children.

17 PATIENT COUNSELING INFORMATION

Advise the patient to read the FDA-approved patient labeling (Medication Guide).

Advise the patient of the potential benefits and risks of ILARIS. Physicians should instruct their patients to read the Medication Guide before starting ILARIS therapy.

Drug Administration

Advise the patient that healthcare providers should perform administration of ILARIS by the subcutaneous injection route [see Dosage and Administration (2.1)].

Infections

Caution the patient that ILARIS use has been associated with serious infections. Counsel the patient to contact their healthcare professional immediately if they develop an infection after starting ILARIS. Treatment with ILARIS should be discontinued if a patient develops a serious infection. Counsel the patient not to take any IL-1 blocking drug, including ILARIS, if they are also taking a drug that blocks TNF, such as etanercept, infliximab, or adalimumab. Use of ILARIS with other IL-1 blocking agents, such as rilonacept and anakinra is not recommended. Caution the patient not to receive ILARIS if they have a chronic or active infection, including HIV, Hepatitis B, or Hepatitis C [see Warnings and Precautions (5.1)].

Vaccinations

Prior to initiation of therapy with ILARIS, physicians should review with adult and pediatric patients their vaccination history relative to current medical guidelines for vaccine use, including taking into account the potential of increased risk of infection during treatment with ILARIS [see Warnings and Precautions (5.4)].

Injection-Site Reactions

Physicians should explain to patients that a very small number of patients in the clinical trials experienced a reaction at the subcutaneous injection site. Injection-site reactions may include pain, erythema, swelling, pruritus, bruising, mass, inflammation, dermatitis, edema, urticaria, vesicles, warmth, and hemorrhage. Healthcare providers should be cautioned to avoid injecting into an area that is already swollen or red. Any persistent reaction should be brought to the attention of the prescribing physician.

Hypersensitivity Reactions

Counsel the patient to stop taking ILARIS and contact their healthcare provider immediately if they develop serious skin reactions or signs of allergic reaction, such as difficulty breathing or swallowing, nausea, dizziness, skin rash, itching, hives, palpitations, or low blood pressure [see Warnings and Precautions (5.3)].

Pregnancy

Advise female patients of the potential risk to a fetus [see Use in Specific Populations (8.1)].

Manufactured by:
Novartis Pharmaceuticals Corporation
East Hanover, New Jersey 07936

US License Number 1244

Distributed by:
Novartis Pharmaceuticals Corporation
East Hanover, New Jersey 07936

© Novartis

T2024-80

Medication Guide
ILARIS® (i-LAHR-us)
(canakinumab)
injection, for subcutaneous use

What is the most important information I should know about ILARIS?
ILARIS can cause serious side effects, including:

- Increased risk of serious infections. ILARIS can lower the ability of your immune system to fight infections. Your healthcare provider should:
  - test you for tuberculosis (TB) before you receive ILARIS.
  - monitor you closely for symptoms of TB during treatment with ILARIS.
  - check you for symptoms of any type of infection before, during, and after your treatment with ILARIS.

Tell your healthcare provider right away if you have any symptoms of an infection, such as fever, sweats or chills, cough, flu-like symptoms, weight loss, shortness of breath, blood in your phlegm, sores on your body, warm or painful areas on your body, diarrhea or stomach pain, or feeling very tired.
See "What are possible side effects of ILARIS?" for more information about side effects.

What is ILARIS?
ILARIS is a prescription medicine injected by your healthcare provider just below the skin (subcutaneous) used to treat:

- The following Periodic Fever Syndromes:
  - Adults and children 4 years of age and older who have auto-inflammatory diseases called Cryopyrin-Associated Periodic Syndromes (CAPS), including:
    - Familial Cold Auto-inflammatory Syndrome (FCAS).
    - Muckle-Wells Syndrome (MWS).
  - Adults and children who have an auto-inflammatory disease called Tumor Necrosis Factor Receptor Associated Periodic Syndrome (TRAPS).
  - Adults and children who have an auto-inflammatory disease called Hyperimmunoglobulin D Syndrome (HIDS) [also known as Mevalonate Kinase Deficiency (MKD)].
  - Adults and children who have an auto-inflammatory disease called Familial Mediterranean Fever (FMF).

- Still’s disease, including Adult-Onset Still’s Disease (AOSD) and Systemic Juvenile Idiopathic Arthritis (SJIA) in children 2 years of age and older.
- Gout flares in adults who:
  - are not able to receive or tolerate treatment with non-steroidal anti-inflammatory drugs (NSAIDS) and colchicine.
  - have not responded to treatment with NSAIDS and colchicine.
  - are not able to receive repeated treatment with steroids.

It is not known if ILARIS is safe and effective when used to treat:

- SJIA in children under 2 years of age.
- CAPS in children under 4 years of age.
- gout flares in children.

Who should not receive ILARIS?

- Do not receive ILARIS if you are allergic to canakinumab or any of the ingredients in ILARIS. See the end of this Medication Guide for a complete list of ingredients in ILARIS.

Before you receive ILARIS, tell your healthcare provider about all your medical conditions, including if you:

- think you have or are being treated for an active infection.
- have symptoms of an infection.
- have a history of infections that keep coming back.
- have a history of low white blood cells.
- have or have had HIV, Hepatitis B, or Hepatitis C.

- have recently received or are scheduled to receive any vaccinations.
  - You should be brought up to date with all age required vaccines before starting treatment with ILARIS.
  - You should not receive ‘live’ vaccines while you are being treated with ILARIS and until your healthcare provider tells you that your immune system is no longer weakened.

- are pregnant or planning to become pregnant. It is not known if ILARIS will harm your unborn baby. Tell your healthcare provider right away if you become pregnant while receiving ILARIS.

- received ILARIS while you were pregnant. It is important that you tell your baby’s healthcare provider before any vaccinations are given to your baby within 4 to 12 months after you received your last dose of ILARIS before giving birth.

- are breastfeeding or planning to breastfeed. It is not known if ILARIS passes into your breast milk. Talk to your healthcare provider about the best way to feed your baby if you receive ILARIS.

Tell your healthcare provider about all the medicines you take, including prescription and over-the-counter medicines, vitamins, and herbal supplements. Especially tell your healthcare provider if you take:

- medicines that affect your immune system.
- medicines called IL-1 blocking agents, such as Kineret® (anakinra), Arcalyst® (rilonacept).
- medicines called Tumor Necrosis Factor (TNF) inhibitors, such as Enbrel® (etanercept), Humira® (adalimumab), Remicade® (infliximab), Simponi® (golimumab), or Cimzia® (certolizumab pegol).
- medicines that affect enzyme metabolism.

Ask your healthcare provider for a list of these medicines if you are not sure.

How should I receive ILARIS?

- ILARIS is given by your healthcare provider as an injection under the skin (subcutaneous injection):
  - every 8 weeks for CAPS.
  - every 4 weeks for TRAPS, HIDS/MKD, FMF, AOSD, and SJIA.
  - as a single dose at the time of a gout flares. If you have a new flare and need another dose of ILARIS, you must wait at least 12 weeks before receiving the next dose.

What are the possible side effects of ILARIS?
ILARIS can cause serious side effects, including:

- See “What is the most important information I should know about ILARIS?”
- decreased ability of your body to fight infections (immunosuppression). For people treated with medicines that cause immunosuppression like ILARIS, the chances of getting cancer may increase.
- serious allergic reactions. Stop taking ILARIS, contact your healthcare provider, and get emergency help right away if you have any of these symptoms of a serious allergic reaction:

◦ swelling of the lips, tongue, mouth, or face
◦ trouble breathing
◦ wheezing
◦ severe itching

◦ skin rash, hives, redness, or swelling outside of the injection site area
◦ dizziness or fainting
◦ fast heartbeat or pounding in your chest (tachycardia)
◦ sweating

- risk of infection with live vaccines. You should not get live vaccines if you are receiving ILARIS. Tell your healthcare provider if you are scheduled to receive any vaccines.

The most common side effects of ILARIS include:
When ILARIS is used for the treatment of CAPS:

• cold symptoms

• headache

• feeling like you are spinning (vertigo)

• diarrhea

• cough

• weight gain

• flu (influenza)

• body aches

• injection-site reactions (such as redness, swelling, warmth, or itching)

• runny nose

• nausea, vomiting, and diarrhea (gastroenteritis)

• nausea

When ILARIS is used for the treatment of TRAPS, HIDS/MKD, and FMF:

• cold symptoms

• runny nose

• nausea, vomiting, and diarrhea (gastroenteritis)

• upper respiratory tract infection

• sore throat

• injection-site reactions (such as redness, swelling, warmth, or itching)

When ILARIS is used for the treatment of Still’s disease (AOSD and SJIA):

• cold symptoms

• runny nose

• nausea, vomiting, and diarrhea (gastroenteritis)

• upper respiratory tract infection

• sore throat

• stomach pain

• pneumonia

• urinary tract infection

• injection-site reactions (such as redness, swelling, warmth, or itching)

When ILARIS is used for the treatment of gout flares:

• cold symptoms

• urinary tract infection

• upper respiratory tract infection

• increased levels of triglycerides in the blood

• back pain

Tell your healthcare provider about any side effect that bothers you or does not go away.
These are not all the possible side effects of ILARIS. For more information, ask your healthcare provider or pharmacist.
Call your doctor for medical advice about side effects. You may report side effects to FDA at 1-800-FDA-1088.

General information about the safe and effective use of ILARIS.
Medicines are sometimes prescribed for purposes other than those listed in this Medication Guide. You can ask your pharmacist or healthcare provider for information about ILARIS that was written for health professionals.

What are the ingredients in ILARIS?
Active ingredient: canakinumab.
Inactive ingredients: Solution for Injection: L-histidine, L-histidine HCl monohydrate, mannitol, polysorbate 80, sterile water for injection.

What are Periodic Fever Syndromes?
Periodic Fever Syndromes is the name for several different autoinflammatory diseases, including CAPS, TRAPS, HIDS/MKD, and FMF. People with these diseases cannot keep certain chemicals made by their body (interleukin-1 beta, also called IL-1β) at the correct level. All these diseases have symptoms that often come and go, with irritated body parts (inflammation) and elevated body temperature (fever). These conditions have a dysregulation of IL-1β production and share similar clinical features of recurrent episodes of inflammation and fever, such as rash, headache, pain (mostly in the joints, belly, eyes, muscles), fatigue, inflammation of other organs, such as heart, lungs, spleen, and brain.
What is Still’s Disease (AOSD and SJIA)?
Still’s disease (which is referred to as AOSD in adults and SJIA in children) is an autoinflammatory disorder which can be caused by having too much or being too sensitive to certain proteins, including interleukin-1 beta (IL-1β), and can lead to symptoms such as fever, rash, headache, feeling very tired (fatigue), or painful joints and muscles.
What is Gout Flare?
A gout flare is caused when a chemical called urate builds-up in the body, and needle-shaped crystals form in and around the joint. These crystals lead to inflammation with excessive production of certain proteins, such as interleukin-1 beta (also called IL-1β), which in turn can lead to sudden, severe pain, redness, warmth and swelling in a joint.
What is Macrophage Activation Syndrome (MAS)?
MAS is a syndrome associated with Still’s disease and some other autoinflammatory diseases like HIDS/MKD that can lead to death. Tell your healthcare provider right away if your AOSD or SJIA symptoms get worse or if you have any of these symptoms of an infection:

- a fever lasting longer than 3 days.
- a cough that does not go away.
- redness in one part of your body.
- warm feeling or swelling of your skin.

Manufactured by:
Novartis Pharmaceuticals Corporation
East Hanover, New Jersey 07936
US License Number 1244
Distributed by: Novartis Pharmaceuticals Corporation, East Hanover, New Jersey 07936
© Novartis
For more information about ILARIS, call 1-888-669-6682 or visit www.ILARIS.com.
Kineret®, Arcalyst®, Enbrel®, Humira®, Remicade®, Simponi®, and Cimzia® are trademarks of Amgen, Regeneron, Immunex Corporation, AbbVie Biotechnology Ltd., Centocor Ortho Biotech Inc., Janssen Biotech Inc., and the UCB Group of companies, respectively.

This Medication Guide has been approved by the U.S. Food and Drug Administration.

Revised: November 2024

T2024-81

PRINCIPAL DISPLAY PANEL

NDC 0078-0734-61

Rx only

ILARIS®
(canakinumab)
Injection

150 mg/mL

For Subcutaneous Use

Single-Dose Vial. Discard Unused portion

Attention: Dispense with enclosed Medication Guide.

NOVARTIS